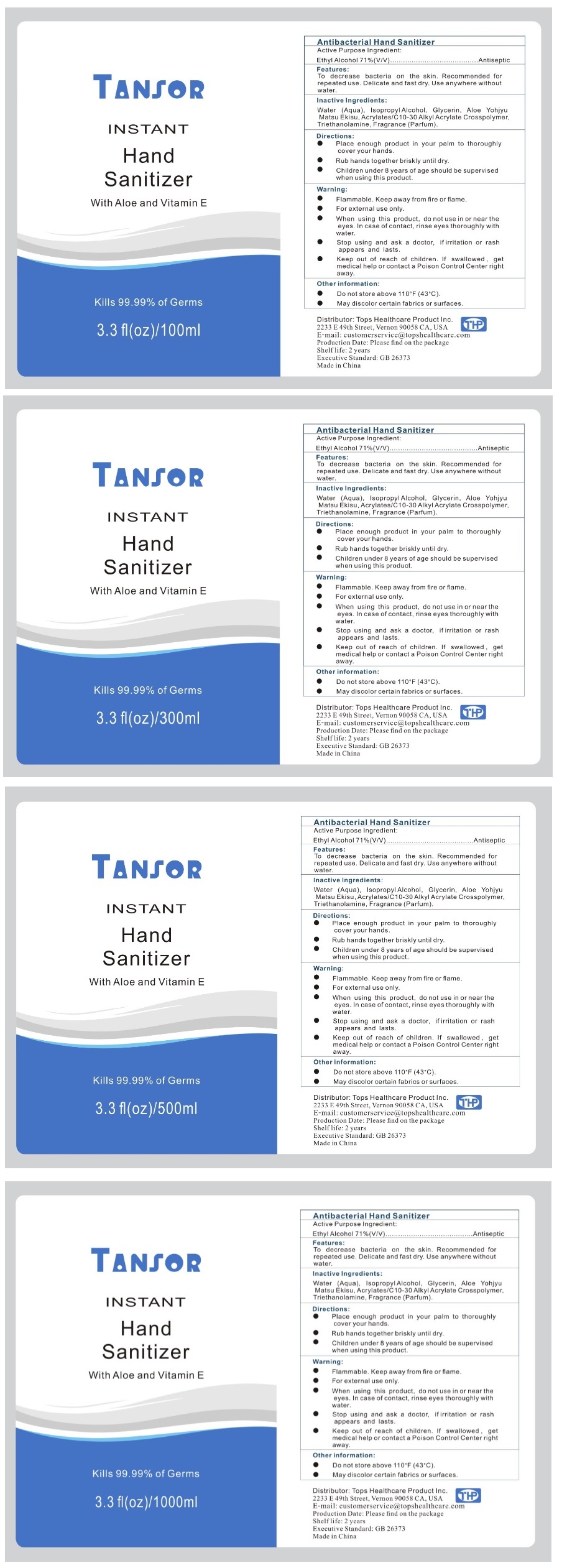 DRUG LABEL: Hand Sanitizer with Aloe and Vitamin E
NDC: 75227-151 | Form: LIQUID
Manufacturer: Top's Healthcare Product Inc
Category: otc | Type: HUMAN OTC DRUG LABEL
Date: 20200416

ACTIVE INGREDIENTS: ALCOHOL 71 mL/100 mL
INACTIVE INGREDIENTS: WATER; ISOPROPYL ALCOHOL; GLYCERIN; ALOE VERA LEAF; CARBOMER INTERPOLYMER TYPE A (ALLYL SUCROSE CROSSLINKED); TROLAMINE

TANSOR INSTANT Hand Sanitizer With Aloe and Vitamin E

Active Ingredient

Ethyl Alcohol 71% (V/V)

Purpose

Antiseptic

Features:

To decrease bacteria on the skin. Recommended for repeated use. Delicate and fast dry. Use anywhere without water.

Inactive Ingredients:

Water (Aqua), Isopropyl Alcohol, Glycerin, Aloe Yohyju Matsu Ekisu, Acrylates/C10-30 Alkyl Acrylate Crosspolymer, Triethanolamine, Fragrance (Parfum).

Directions:

- Place enough product in your palm to thoroughly cover your hands.
- Rub hands together briskly until dry.
- Children under 8 years of age should be supervised when using this product.

Warning:

- Flammable. Keep away from fire or flame.
- For external use only.
- When using this product, do not use in or near the eyes. In case of contact, rinse eyes thoroughly with water.
- Stop using and ask a doctor, if irritation or rash appears and lasts.

- Keep out of reach of children. If swallowed, get medical help or contact a Poison Control Center right away.

Other information:

- Do not store above 110°F (43°C).
- May discolor certain fabrics or surfaces.

Kills 99.99% of Germs

Distributor: Tops Healthcare Product Inc.

2233 E 49th Street, Vernon 90058 CA, USA THP

E-mail: customerservice@topshealthcare.com

Production Date: Please find on the package

Shelf life: 2 years

Executive Standard: GB 26373

Made in China